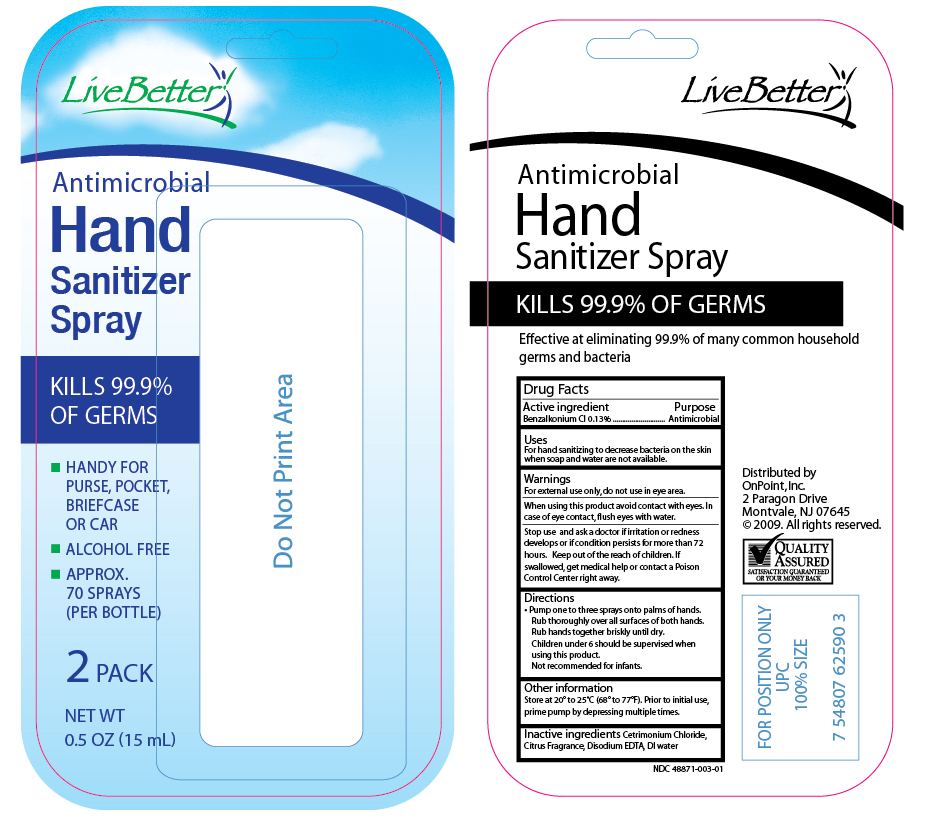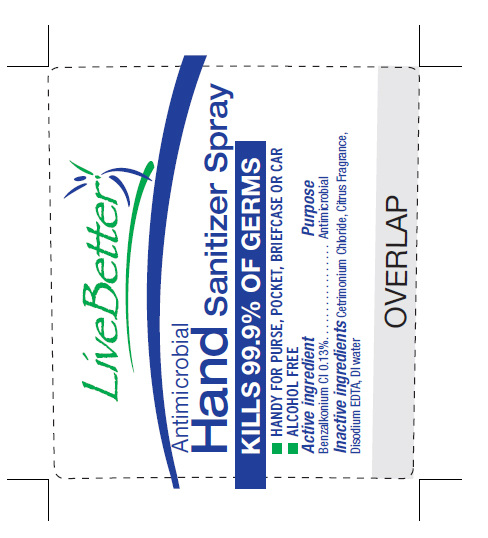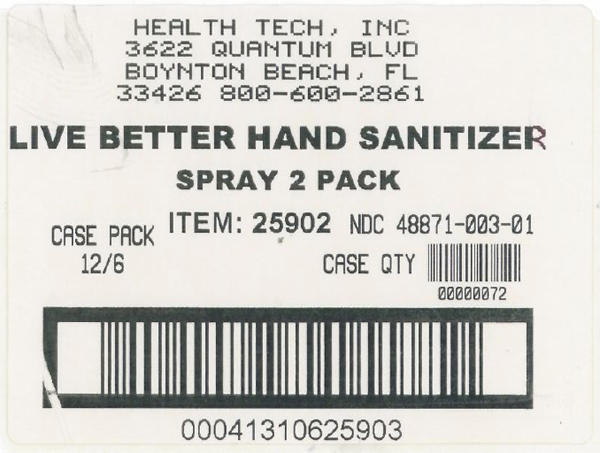 DRUG LABEL: Live Better 
NDC: 48871-003 | Form: SPRAY
Manufacturer: Health-Tech, Inc.
Category: otc | Type: HUMAN OTC DRUG LABEL
Date: 20100525

ACTIVE INGREDIENTS: Benzalkonium Chloride .0013 mL/1 mL
INACTIVE INGREDIENTS: Cetrimonium Chloride; Edetate disodium; water

Drug Facts

Active Ingredient

Benzalkonium Chloride

PURPOSE

Antimicrobial

Warnings

For external use only, do not use in the eye area.

When using this product

- avoid contact with eyes
- in case of eye contact flush eyes with water

Stop use and ask a doctor if

- irritation or redness develops or
- if condition persists for more than 72 hours

Keep out of reach of children

If swallowed, get medical help or contact a Poison Control Center right away.

Directions

- Pump one to three sprays onto palms of hands
- Rub thoroughly over all surfaces of both hands
- Rub hands together briskly until dry
- Children under 6 should be supervised when using this product
- Not recommended for infants

Other information

- Store between 20^0 to 25^0 C (68^0 to 77^0 F)
- Prior to initial use, prime pump by depressing multiple times

Inactive Ingredients

Cetrimonium Chloride, Citrus Fragrance, Disodium EDTA, DI Water

PACKAGE LABEL

MM12

PACKAGE LABEL

MM13

PACKAGE LABEL

MM14